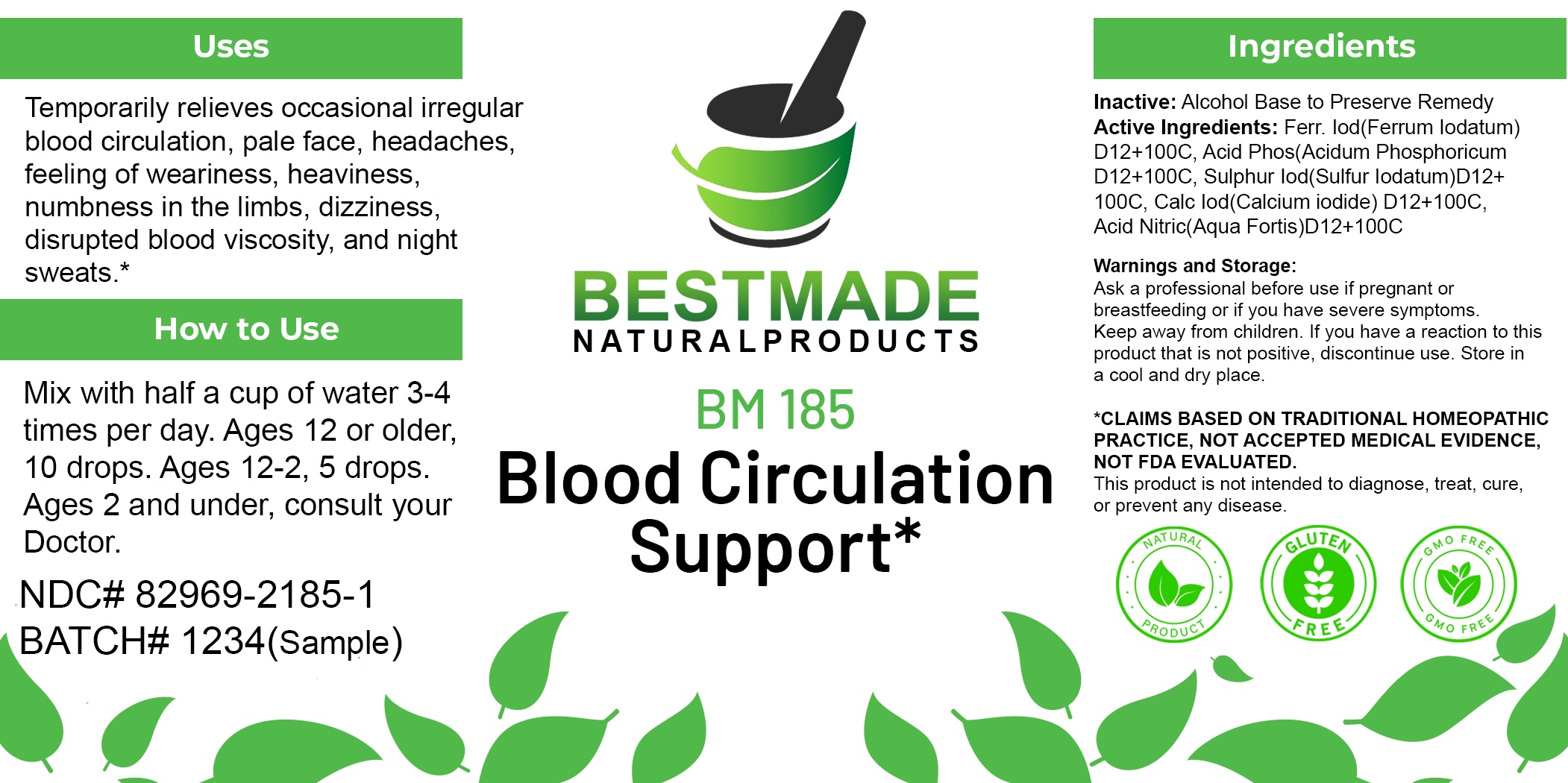 DRUG LABEL: Bestmade Natural Products BM185
NDC: 82969-2185 | Form: LIQUID
Manufacturer: Bestmade Natural Products
Category: homeopathic | Type: HUMAN OTC DRUG LABEL
Date: 20250220

ACTIVE INGREDIENTS: NITRIC ACID 30 [hp_C]/30 [hp_C]; PHOSPHORIC ACID 30 [hp_C]/30 [hp_C]; FERROUS IODIDE 30 [hp_C]/30 [hp_C]; SULFUR IODIDE 30 [hp_C]/30 [hp_C]; CALCIUM IODIDE 30 [hp_C]/30 [hp_C]
INACTIVE INGREDIENTS: ALCOHOL 30 [hp_C]/30 [hp_C]

BM185

DOSAGE AND ADMINISTRATION

How to Use

Mix with half a cup of water 3-4 times per day. Ages 12 or older, 10 drops. Ages 12-2, 5 drops. Ages 2 and under, consult your Doctor.

Inactive:

Alcohol Base to Preserve Product

ACTIVE INGREDIENTS
Ferr. IodD12 100C, Acid PhosD12 100C, Sulphur IodD12 100C, Calc IodD12 100C, Acid NitricD12 100C

KEEP OUT OF REACH OF CHILDREN

Warnings and Storage:

Ask a professional before use if pregnant or breastfeeding or if you have severe symptoms.

Keep away from children. If you have a reaction to this product that is not positive, discontinue use. Store in a cool and dry place

*CLAIMS BASED ON TRADITIONAL HOMEOPATHIC PRACTICE, NOT ACCEPTED MEDICAL EVIDENCE NOT FDA EVALUATED.
This product is not intended to diagnose, treat, cure, or prevent any disease.

Warnings and Storage:

Ask a professional before use if pregnant or breastfeeding or if you have severe symptoms.

Keep away from children. If you have a reaction to this product that is not positive, discontinue use. Store in a cool and dry place

*CLAIMS BASED ON TRADITIONAL HOMEOPATHIC PRACTICE, NOT ACCEPTED MEDICAL EVIDENCE NOT FDA EVALUATED.
This product is not intended to diagnose, treat, cure, or prevent any disease.

Use:

Temporarily relieves occasional irregular blood circulation, pale face, headaches, feeling of weariness, heaviness, numbness in the limbs, dizziness, disrupted blood viscosity, and night sweats.*

Use:

Temporarily relieves occasional irregular blood circulation, pale face, headaches, feeling of weariness, heaviness, numbness in the limbs, dizziness, disrupted blood viscosity, and night sweats.*

Entire package label